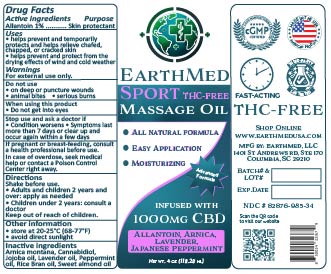 DRUG LABEL: Earthmed FS massage oil
NDC: 82876-986 | Form: OIL
Manufacturer: Earthmed LLC
Category: otc | Type: HUMAN OTC DRUG LABEL
Date: 20250805

ACTIVE INGREDIENTS: ALLANTOIN 1 g/108.48 g
INACTIVE INGREDIENTS: RICE BRAN OIL 65.235 g/108.48 g; LAVENDER OIL 0.28 g/108.48 g; PEPPERMINT OIL 0.15 g/108.48 g; ARNICA MONTANA FLOWER WATER 2.85 g/108.48 g; ALMOND OIL 27.2 g/108.48 g; JOJOBA OIL 10.58 g/108.48 g; CANNABIDIOL 1.13 g/108.48 g; .DELTA.9-TETRAHYDROCANNABINOLIC ACID 0.055 g/108.48 g

Earthmed FS Massage Oil

Active ingredients

Allantoin......1%

Purpose

Skin protectant

Uses

Helps prevent and temporarily protect and help relieve chafed, chapped, or cracked skin.

Helps prevent and protect from the drying of wind and cold weather

Warnings

For external use only.

Do not use

on deep or puncture wounds, animal bites, serious burns

When using this product

Do not get into eyes

Stop use and ask doctor if

condition worsens, symptoms last for more than 7 days, condition clears up but occurs again within a few days, rash or irritation occurs

Stop use and ask doctor if

Condition worsens, Symptoms last for more than 7 days, condition clears up but occurs again in a few days, rash or irritation occurs

If pregnant or breast feeding

Consult a health professional before use.

in case of overdose

seek medical help or contact a poison control center right away

Directions

shake well before use.

adults and children 2 years and over; apply as needed.

children under 2 years; consult a doctor

keep out of reach of children

Other information

Store at 68-77 degrees F (20-25 degrees C), avoid direct sunlight

inactive ingredients

Arnica montana, Cannabidiol, Jojoba oil, Lavender oil, Peppermint oil, Rice bran oil, Sweet almond oil.